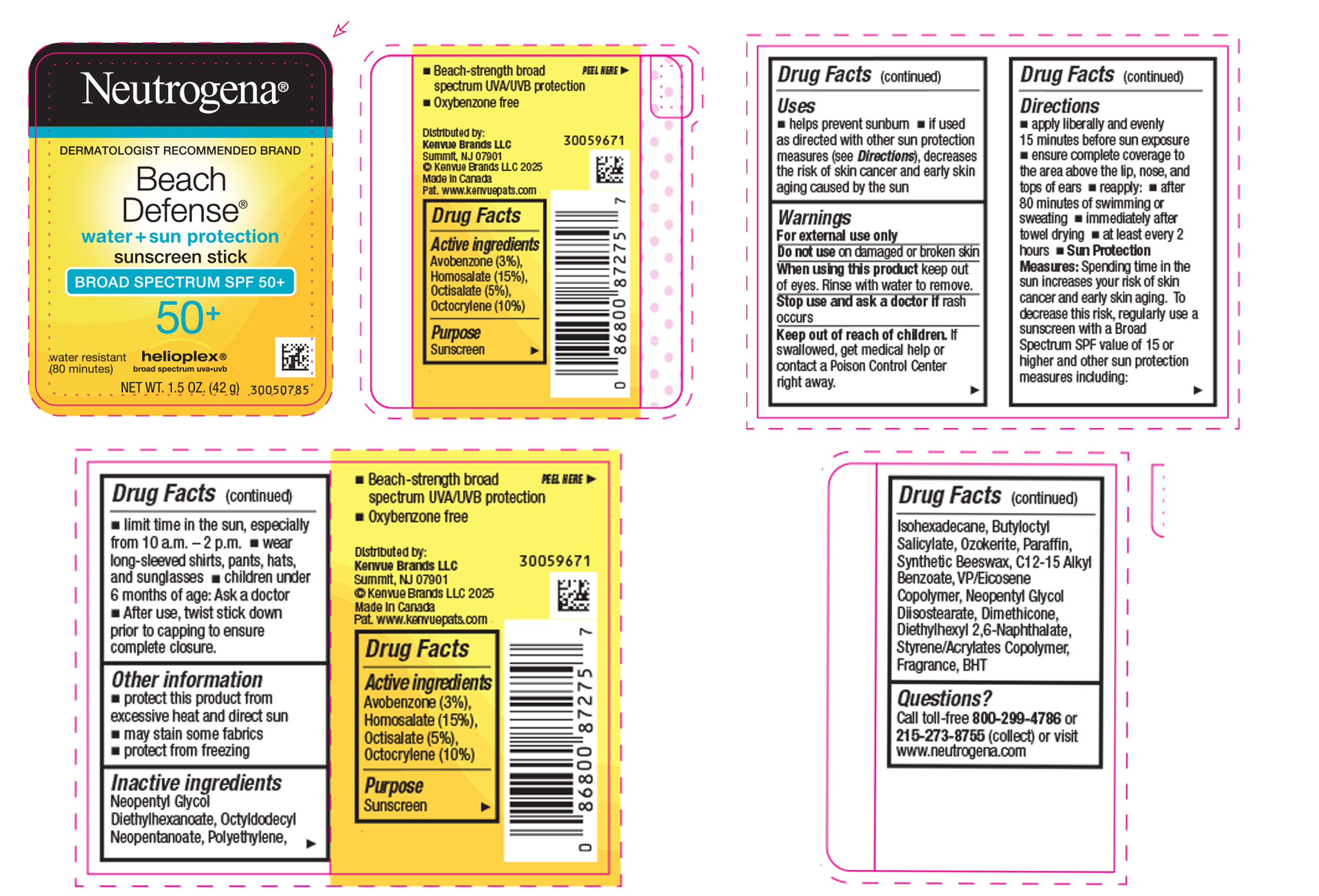 DRUG LABEL: Neutrogena Beach Defense Water Plus Sun Protection Sunscreen Broad Spectrum SPF 50 Plus
NDC: 69968-0899 | Form: STICK
Manufacturer: Kenvue Brands LLC
Category: otc | Type: HUMAN OTC DRUG LABEL
Date: 20250825

ACTIVE INGREDIENTS: AVOBENZONE 30 mg/1 g; HOMOSALATE 150 mg/1 g; OCTISALATE 50 mg/1 g; OCTOCRYLENE 100 mg/1 g
INACTIVE INGREDIENTS: POLYETHYLENE; OCTYLDODECYL NEOPENTANOATE; ISOHEXADECANE; BUTYLOCTYL SALICYLATE; CERESIN; PARAFFIN; ALKYL (C12-15) BENZOATE; NEOPENTYL GLYCOL DIISOSTEARATE; DIMETHICONE; DIETHYLHEXYL 2,6-NAPHTHALATE; BUTYLATED HYDROXYTOLUENE; EICOSYL POVIDONE; SYNTHETIC BEESWAX; NEOPENTYL GLYCOL DIETHYLHEXANOATE; BUTYL METHACRYLATE/METHYL METHACRYLATE/METHACRYLIC ACID/STYRENE CROSSPOLYMER

Neutrogena® Beach Defense® water + sun protection sunscreen stick BROAD SPECTRUM SPF 50+

Drug Facts

ACTIVE INGREDIENT

Active ingredients | Purpose
Avobenzone 3% | Sunscreen
Homosalate 15% | Sunscreen
Octisalate 5% | Sunscreen
Octocrylene 10% | Sunscreen

Uses

- helps prevent sunburn
- if used as directed with other sun protection measures (see Directions), decreases the risk of skin cancer and early skin aging caused by the sun

Warnings

For external use only

Do not use on damaged or broken skin

When using this product keep out of eyes. Rinse with water to remove.

Stop use and ask a doctor if rash occurs

Keep out of reach of children. If swallowed, get medical help or contact a Poison Control Center right away.

Directions

- apply liberally and evenly 15 minutes before sun exposure
- ensure complete coverage to the area above the lip, nose and tops of ears
- reapply:
- after 80 minutes of swimming or sweating
- immediately after towel drying
- at least every 2 hours
- Sun Protection Measures. Spending time in the sun increases your risk of skin cancer and early skin aging. To decrease this risk, regularly use a sunscreen with a Broad Spectrum SPF value of 15 or higher and other sun protection measures including:
- limit time in the sun, especially from 10 a.m. – 2 p.m.
- wear long-sleeved shirts, pants, hats, and sunglasses
- children under 6 months of age: Ask a doctor
- After use, twist stick down prior to capping to ensure complete closure.

Other information

- protect this product from excessive heat and direct sun
- may stain some fabrics
- protect from freezing

Inactive ingredients

Neopentyl Glycol Diethylhexanoate, Octyldodecyl Neopentanoate, Synthetic Wax, Isohexadecane, Butyloctyl Salicylate, Ozokerite, Paraffin, Synthetic Beeswax, C12-15 Alkyl Benzoate, VP/Eicosene Copolymer, Neopentyl Glycol Diisostearate, Dimethicone, Diethylhexyl 2,6-Naphthalate, Styrene/Acrylates Copolymer, Fragrance, BHT

Questions?

Call toll‐free 800-299-4786 or 215‐273‐8755 (collect) or visit www.neutrogena.com

Distributed by:
Kenvue Brands LLC
Summit, NJ 07901

PRINCIPAL DISPLAY PANEL - 42 g Canister Label

Neutrogena®
DERMATOLOGIST RECOMMENDED BRAND
Beach
Defense®
water + sun protection
sunscreen stick
BROAD SPECTRUM SPF 50+

50+
helioplex®
broad spectrum uva•uvb
water resistant (80minutes)
NET WT. 1.5 OZ. (42 g)